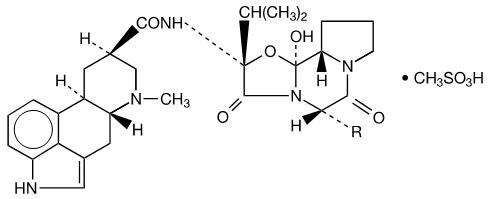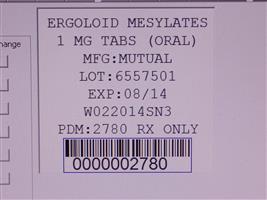 DRUG LABEL: Ergoloid Mesylates
NDC: 68151-2780 | Form: TABLET
Manufacturer: Carilion Materials Management
Category: prescription | Type: HUMAN PRESCRIPTION DRUG LABEL
Date: 20160804

ACTIVE INGREDIENTS: DIHYDROERGOCORNINE MESYLATE 0.333 mg/1 1; DIHYDROERGOCRISTINE MESYLATE 0.333 mg/1 1; DIHYDRO-.ALPHA.-ERGOCRYPTINE MESYLATE 0.222 mg/1 1; DIHYDRO-.BETA.-ERGOCRYPTINE MESYLATE 0.111 mg/1 1
INACTIVE INGREDIENTS: butylated hydroxyanisole; starch, corn; hydrogenated cottonseed oil; lactose; mannitol; povidone k90; stearic acid; talc

ERGOLOID MESYLATES
TABLETS USP
(ORAL)

Rx only

DESCRIPTION

Each tablet for oral use contains ergoloid mesylates USP; a mixture of the methanesulfonate salt of the following hydrogenated alkaloids:

 | R
Dihydroergocornine | -CH(CH3)2
Dihydroergocristine | -CH2C6H5
Dihydro-α-ergocryptine | -CH2CH(CH3)2
Dihydro-β-ergocryptine | -CH(CH3)CH2CH3

C31H41N5O5 • CH4O3S (dihydroergocornine mesylate)
659.79

C35H41N5O5 • CH4O3S (dihydroergocristine mesylate)
707.84

C32H43N5O5 • CH4O3S (dihydro-α-ergocryptine mesylate)
673.82

C32H43N5O5 • CH4O3S (dihydro-β-ergocryptine mesylate)
673.82

 | 1 mg
Dihydroergocristine mesylate | 0.333 mg
Dihydroergocornine mesylate | 0.333 mg
Dihydroergocryptine mesylate [exists as a mixture of alpha and beta isomers in a ratio of 2:1] | 0.333 mg

Inactive ingredients for oral tablets are: butylated hydroxyanisol, corn starch, hydrogenated vegetable oil, lactose, mannitol, polyvinyl pyrrolidone, stearic acid and talc.

CLINICAL PHARMACOLOGY

There is no specific evidence which clearly establishes the mechanism by which ergoloid mesylates preparations produce mental effects, nor is there conclusive evidence that the drug particularly affects cerebral arteriosclerosis or cerebrovascular insufficiency.

Pharmacokinetic Properties

Pharmacokinetic studies have been performed in normal volunteers with the help of radiolabelled drug as well as employing a specific radioimmunoassay technique. From the urinary excretion quotient of orally and intravenously administered tritium-labelled ergoloid mesylates the absorption of ergoloid was calculated to be 25%. Following oral administration, peak levels of 0.5 ngEq/mL/mg were achieved within 1.5–3 hr. Bioavailability studies with the specific radioimmunoassay confirm that ergoloid is rapidly absorbed from the gastrointestinal tract, with mean peak levels of 0.05–0.13 ng/mL/mg (with extremes of 0.03 and 0.18 ng/mL/mg) achieved within 0.6–1.3 hr (with extremes of 0.4 and 2.8 hr). The finding of lower peak levels of ergoloid compared to the total drug-metabolite composite is consistent with a considerable first pass liver metabolism, with less than 50% of the therapeutic moiety reaching the systemic circulation. The elimination of radioactivity, representing ergoloid plus metabolites bearing the radiolabel, was biphasic with half-lives of 4 and 13 hr. The mean half-life of unchanged ergoloid in plasma is about 2.6–5.1 hr; after 3 half-lives ergoloid plasma levels are less than 10% of radioactivity levels, and by 24 hr no ergoloid is detectable.

Bioequivalence studies were performed comparing ergoloid mesylates oral tablets (administered orally) with ergoloid mesylates sublingual tablets (administered sublingually). The oral tablet and sublingual tablet were shown to be bioequivalent.

INDICATIONS

A proportion of individuals over sixty who manifest signs and symptoms of an idiopathic decline in mental capacity (i.e., cognitive and interpersonal skills, mood, self-care, apparent motivation) can experience some symptomatic relief upon treatment with ergoloid mesylates preparations. The identity of the specific trait(s) or condition(s), if any, which would usefully predict a response to ergoloid mesylates therapy is not known. It appears, however, that those individuals who do respond come from groups of patients who would be considered clinically to suffer from some ill-defined process related to aging or to have some underlying dementing condition (i.e., primary progressive dementia, Alzheimer's dementia, senile onset, multi-infarct dementia).

Before prescribing ergoloid mesylates, the physician should exclude the possibility that the patient's signs and symptoms arise from a potentially reversible and treatable condition. Particular care should be taken to exclude delirium and dementiform illness secondary to systemic disease, primary neurological disease, or primary disturbance of mood. Ergoloid mesylates preparations are not indicated in the treatment of acute or chronic psychosis, regardless of etiology (see CONTRAINDICATIONS).

The decision to use ergoloid mesylates in the treatment of an individual with a symptomatic decline in mental capacity of unknown etiology should be continually reviewed since the presenting clinical picture may subsequently evolve sufficiently to allow a specific diagnosis and a specific alternative treatment. In addition, continued clinical evaluation is required to determine whether any initial benefit conferred by ergoloid mesylates therapy persists with time.

The efficacy of ergoloid mesylates was evaluated using a special rating scale known as the SCAG (Sandoz Clinical Assessment-Geriatric). The specific items on this scale on which modest but statistically significant changes were observed at the end of twelve weeks include: mental alertness, confusion, recent memory, orientation, emotional lability, self-care, depression, anxiety/fears, cooperation, sociability, appetite, dizziness, fatigue, bothersome(ness), and an overall impression of clinical status.

CONTRAINDICATIONS

Ergoloid mesylates preparations are contraindicated in individuals who have previously shown hypersensitivity to the drug. Ergoloid mesylates preparations are also contraindicated in patients who have psychosis, acute or chronic, regardless of etiology.

PRECAUTIONS

Practitioners are advised that because the target symptoms are of unknown etiology, careful diagnosis should be attempted before prescribing ergoloid mesylates preparations.

ADVERSE REACTIONS

Ergoloid mesylates preparations have not been found to produce serious side effects. Transient nausea and gastric disturbances have been reported. Ergoloid mesylates preparations do not possess the vasoconstrictor properties of the natural ergot alkaloids.

DOSAGE AND ADMINISTRATION

1 mg three times a day.

Alleviation of symptoms is usually gradual and results may not be observed for 3–4 weeks.

HOW SUPPLIED

Product: 68151-2780

NDC: 68151-2780-0 1 TABLET in a PACKAGE

Distributed by: Sun Pharmaceutical Industries, Inc.
Cranbury, NJ 08512

Rev 02, August 2014